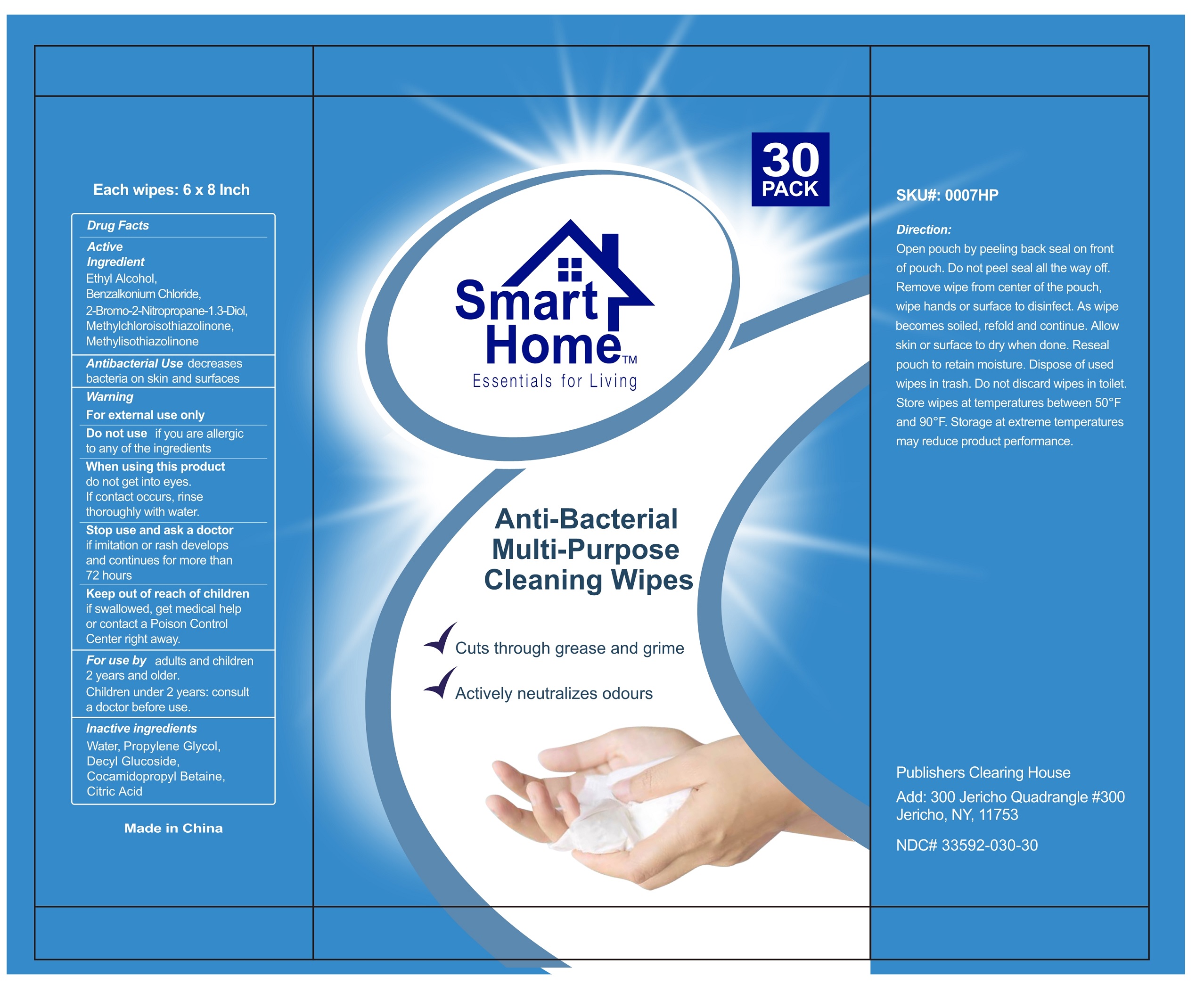 DRUG LABEL: Anti-Bacterial Multi-Purpose Cleaning Wipes
NDC: 78122-030 | Form: CLOTH
Manufacturer: Wenzhou Guanshang Paper Co., Ltd
Category: otc | Type: HUMAN OTC DRUG LABEL
Date: 20200803

ACTIVE INGREDIENTS: ALCOHOL 0.4 mL/100 1; BENZALKONIUM CHLORIDE 150 mg/100 1; BRONOPOL 50 mg/100 1; METHYLCHLOROISOTHIAZOLINONE 0.9 mg/100 1; METHYLISOTHIAZOLINONE 0.3 mg/100 1
INACTIVE INGREDIENTS: DECYL GLUCOSIDE; COCAMIDOPROPYL BETAINE; CITRIC ACID MONOHYDRATE; WATER; PROPYLENE GLYCOL

78122-030 Guanshang, anti-bacterial multi-purpose cleaning Wipes, Publishers Clearing House 33592-030

Active ingredient

Alcohol,Benzalkonium Chloride,2-Bromo-2-Nitropropane-1.3-Diol,Methylchloroisothiazolinone,Methylisothiazolinone.

Purpose

Antibacterial Use decreases bacteria on skin and surfaces.

When using

When using this product:

do not get into eyes.

if contact occurs,rinse thoroughly with water.

Do not use

if you are allergic to any of the ingredients.

Stop use

Stop use if irritation or rash develops and continues for more than 72 hours.

Keep out of reach of children

If swallowed, get medical help or contact a Poison Control Center right away.

Indications & usage

For use by adults and children 2 years and older.
Children under 2 years: consult a doctor before use.

Directions

Open pouch by peeling back seal on front of pouch. Do not peel seal all the way off. Remove wipe from center of the pouch, ready to use. As wipe becomes soiled, refold and continue.Reseal pouch to retain moisture.Dispose of used wipes in trash.Do not discard wipes in toilet.Store wipes at temperatures between 50℉ and 90℉.Storage at extreme temperatures may reduce product performance.

Warnings

For external use only.

Other information

Open pouch by peeling back seal on front of pouch. Do not peel seal all the way off. Remove wipe from center of the pouch, ready to use. As wipe becomes soiled, refold and continue.Reseal pouch to retain moisture.Dispose of used wipes in trash.Do not discard wipes in toilet.Store wipes at temperatures between 50℉ and 90℉.Storage at extreme temperatures may reduce product performance.

Inactive ingredient

Water,Propylene Glycol,Decyl Glucoside,Cocamidopropyl Betaine,Citric Acid.

Package label. Principal display panel

30 cloth in 1 package NDC:78122-030-30